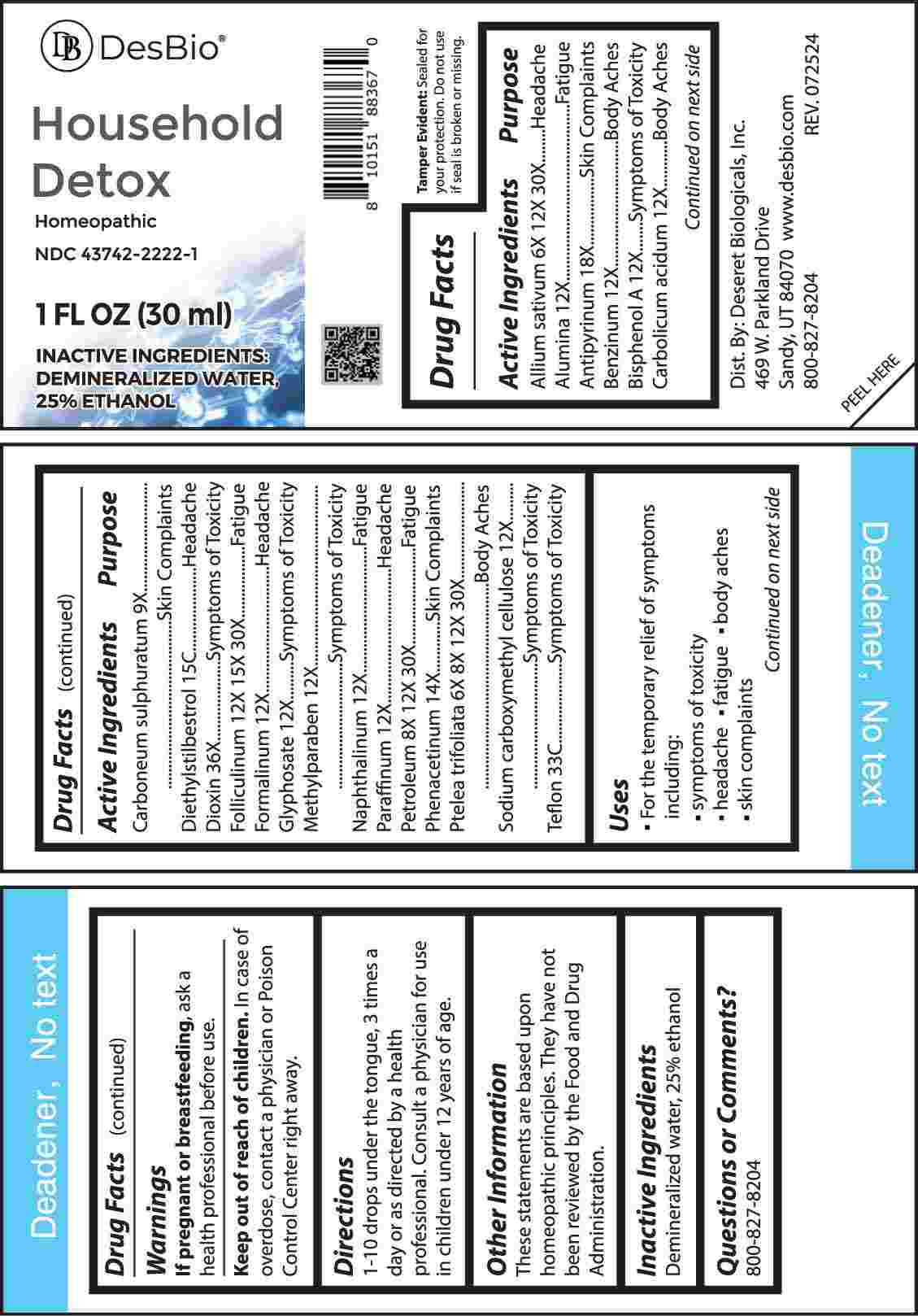 DRUG LABEL: Household Detox
NDC: 43742-2222 | Form: LIQUID
Manufacturer: Deseret Biologicals, Inc.
Category: homeopathic | Type: HUMAN OTC DRUG LABEL
Date: 20241213

ACTIVE INGREDIENTS: GARLIC 6 [hp_X]/1 mL; ALUMINUM OXIDE 12 [hp_X]/1 mL; ANTIPYRINE 18 [hp_X]/1 mL; BENZENE 12 [hp_X]/1 mL; BISPHENOL A 12 [hp_X]/1 mL; PHENOL 12 [hp_X]/1 mL; CARBON DISULFIDE 9 [hp_X]/1 mL; DIETHYLSTILBESTROL 15 [hp_C]/1 mL; 2,3,7,8-TETRACHLORODIBENZO-P-DIOXIN 36 [hp_X]/1 mL; ESTRONE 12 [hp_X]/1 mL; FORMALDEHYDE SOLUTION 12 [hp_X]/1 mL; GLYPHOSATE 12 [hp_X]/1 mL; METHYLPARABEN 12 [hp_X]/1 mL; NAPHTHALENE 12 [hp_X]/1 mL; PARAFFIN 12 [hp_X]/1 mL; KEROSENE 8 [hp_X]/1 mL; PHENACETIN 14 [hp_X]/1 mL; PTELEA TRIFOLIATA BARK 6 [hp_X]/1 mL; CARBOXYMETHYLCELLULOSE SODIUM, UNSPECIFIED 12 [hp_X]/1 mL; POLYTETRAFLUOROETHYLENE 33 [hp_C]/1 mL
INACTIVE INGREDIENTS: WATER; ALCOHOL

DRUG FACTS:

ACTIVE INGREDIENTS:

Allium Sativum 6X, 12X, 30X, Alumina 12X, Antipyrinum 18X, Benzinum 12X, Bisphenol A 12X, Carbolicum Acidum 12X, Carboneum Sulphuratum 9X, Diethylstilbestrol 15C, Dioxin 36X, Folliculinum 12X, 15X, 30X, Formalinum 12X, Glyphosate 12X, Methylparaben 12X, Naphthalinum 12X, Paraffinum 12X, Petroleum 8X, 12X, 30X, Phenacetinum 14X, Ptelea Trifoliata 6X, 8X, 12X, 30X, Sodium Carboxymethyl Cellulose 12X, Teflon 33C.

PURPOSE:

Allium Sativum - Headache, Alumina - Fatigue, Antipyrinum – Skin Complaints, Benzinum – Body Aches, Bisphenol A – Symptoms of Toxicity, Carbolicum Acidum – Body Aches, Carboneum Sulphuratum – Skin Complaints, Diethylstilbestrol - Headache, Dioxin – Symptoms of Toxicity, Folliculinum - Fatigue, Formalinum - Headache, Glyphosate – Symptoms of Toxicity, Methylparaben – Symptoms of Toxicity, Naphthalinum - Fatigue, Paraffinum - Headache, Petroleum - Fatigue, Phenacetinum – Skin Complaints, Ptelea Trifoliata – Body Aches, Sodium Carboxymethyl Cellulose - Symptoms of Toxicity, Teflon - Symptoms of Toxicity

USES:

• For the temporary relief of symptoms including:

• symptoms of toxicity • headache

• fatigue • body aches • skin complaints

These statements are based upon homeopathic principles. They have not been reviewed by the Food and Drug Administration.

WARNINGS:

If pregnant or breastfeeding, ask a health professional before use.

Keep out of reach of children. In case of overdose, contact a physician or Poison Control Center right away.

Tamper Evident: Sealed for your protection. Do not use if seal is broken or missing.

KEEP OUT OF REACH OF CHILDREN:

In case of overdose, contact a physician or Poison Control Center right away.

DIRECTIONS:

1-10 drops under the tongue, 3 times a day or as directed by a health professional. Consult a physician for use in children under 12 years of age.

INACTIVE INGREDIENTS:

Demineralized water, 25% ethanol

QUESTIONS:

Dist. By: Deseret Biologicals, Inc.
469 W. Parkland Drive
Sandy, UT 84070

www.desbio.com

800-827-8204

PACKAGE LABEL DISPLAY:

DesBio

Household Detox

Homeopathic

NDC 43742-2222-1

1 FL OZ (30 ml)